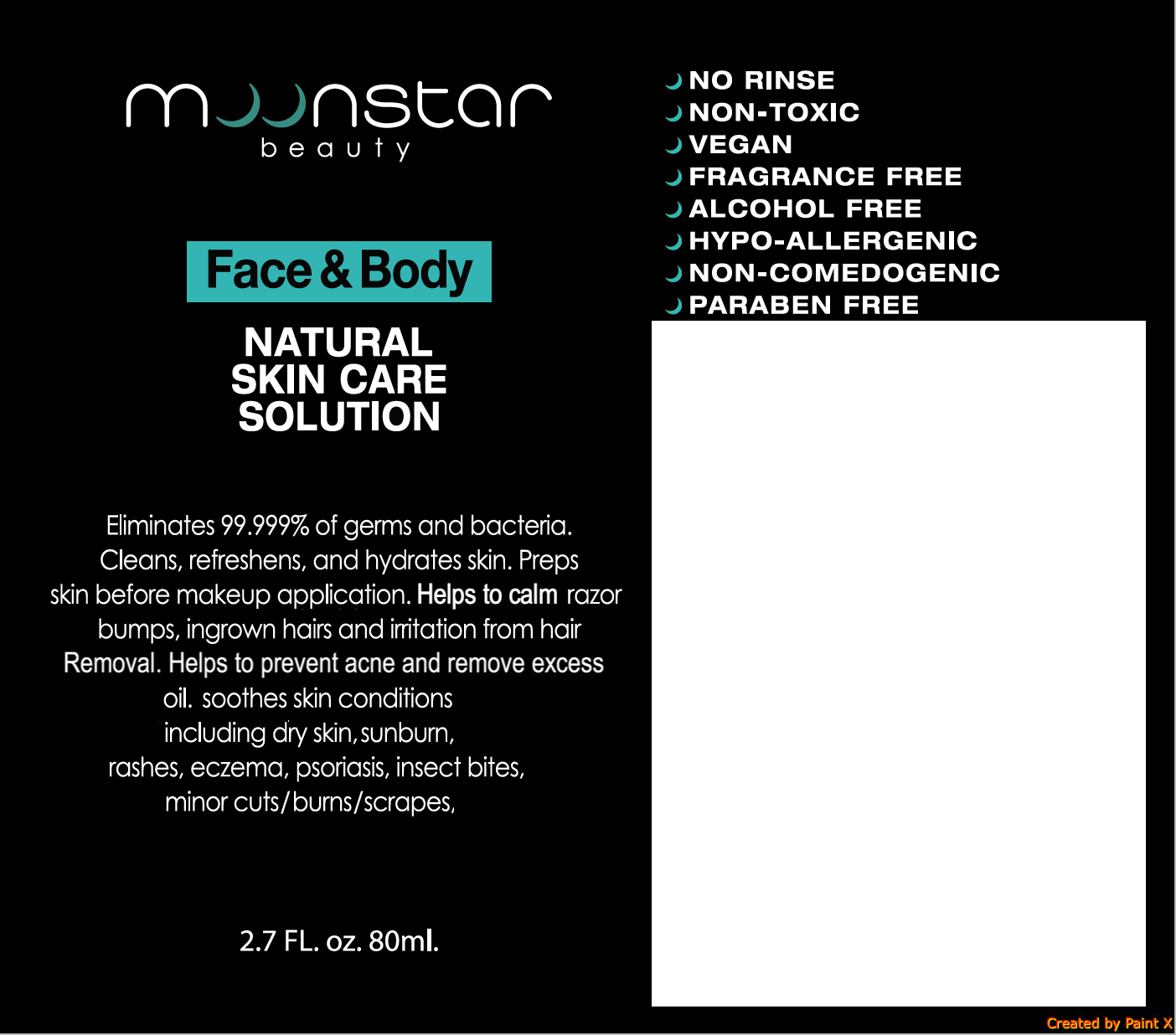 DRUG LABEL: MOONSTAR FACE AND BODY MIST
NDC: 72111-100 | Form: SPRAY
Manufacturer: NATURAL ETHICS, INC.
Category: otc | Type: HUMAN OTC DRUG LABEL
Date: 20180222

ACTIVE INGREDIENTS: POTASSIUM CARBONATE 0.08 g/80 mL
INACTIVE INGREDIENTS: HYPROMELLOSES; WATER; CITRIC ACID MONOHYDRATE; CALCIUM HYDROXIDE

MOONSTAR FACE & BODY MIST

Active ingredients

Potassium carbonate (0.1%)

Purpsoe

antibacterial

Uses

Sanitizer to help decrease bacteria on skin. Helps to soothe skin.

Warnings

For external use only

Do not use when skin is red, inflamed, irritated, or painful

When using this product

- do not use on damaged or broken skin
- avoid contact with eyes. If contact occurs, rinse eyes thoroughly with water
- do not apply directly to wound or open cut

Stop use and ask a doctor if

- Rash or irritation on skin develops and lasts

Keep out of reach of children

If swallowed, get medical help or contact a Poison Control Center (1-800-222-1222) right away.

DIrections

Spray daily on face and body to cleanse and refreshes skin. Safe for use on sensitive areas of the body.

Inactive ingredients

Distilled water, Hydroxypropylmethyl Cellulose, Citric Acid, Tea Catechin, Calcium hydroxide